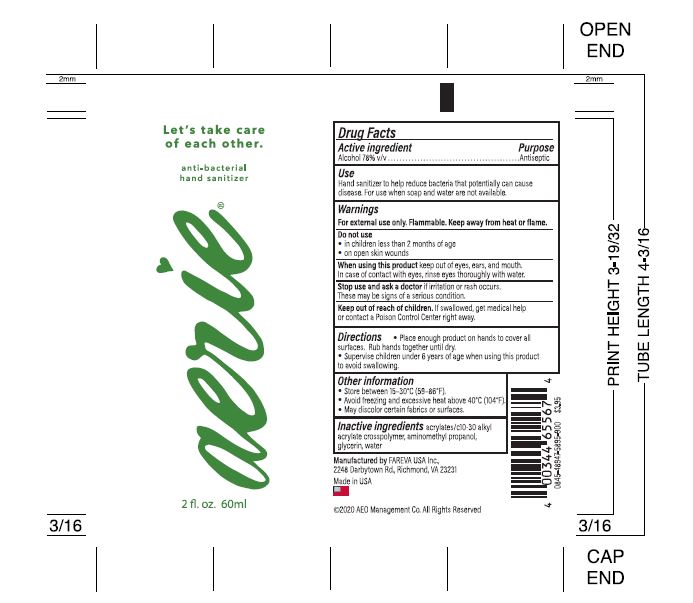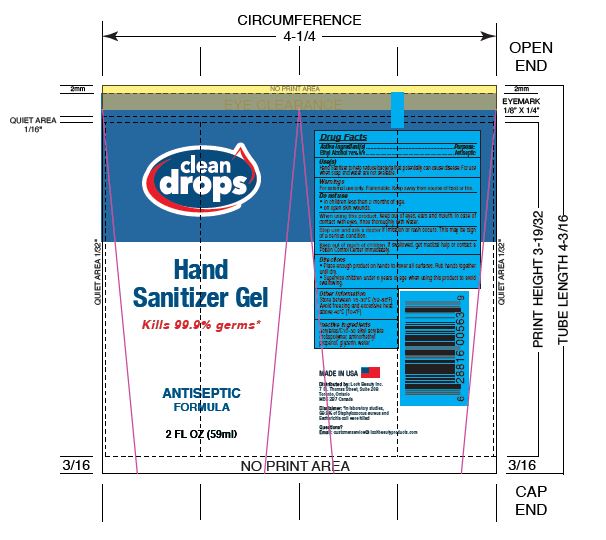 DRUG LABEL: Hand Sanitizer
NDC: 72686-182 | Form: GEL
Manufacturer: Fareva Morton Grove, Inc.
Category: otc | Type: HUMAN OTC DRUG LABEL
Date: 20201029

ACTIVE INGREDIENTS: ALCOHOL 78 mL/100 mL
INACTIVE INGREDIENTS: AMINOMETHYLPROPANOL; GLYCERIN; CARBOMER INTERPOLYMER TYPE A (ALLYL SUCROSE CROSSLINKED); WATER

1. Alcohol (ethanol) (USP or Food Chemical Codex (FCC) grade) (78%, volume/volume (v/v)) in an aqueous solution denatured according to Alcohol and Tobacco Tax and Trade Bureau regulations in 27 CFR part 20.
2. Glycerin
3. Acrylates/C10-30 Alkyl Acrylate Crosspolymer
4. Aminomethyl propanol
5. Water

The firm does not add other active or inactive ingredients. Different or additional ingredients may impact the quality and potency of the product.

Active Ingredient(s)

Alcohol 78% v/v. Purpose: Antiseptic

Purpose

Antiseptic, Hand Sanitizer

Use

Hand Sanitizer to help reduce bacteria that potentially can cause disease. For use when soap and water are not available.

Warnings

For external use only. Flammable. Keep away from heat or flame

Do not use

- in children less than 2 months of age
- on open skin wounds

When using this product keep out of eyes, ears, and mouth. In case of contact with eyes, rinse eyes thoroughly with water.
Stop use and ask a doctor if irritation or rash occurs. These may be signs of a serious condition.
Keep out of reach of children. If swallowed, get medical help or contact a Poison Control Center right away.

Stop use and ask a doctor if irritation or rash occurs. These may be signs of a serious condition.

Keep out of reach of children. If swallowed, get medical help or contact a Poison Control Center right away.

Directions

- Place enough product on hands to cover all surfaces. Rub hands together until dry.
- Supervise children under 6 years of age when using this product to avoid swallowing.

Other information

- Store between 15-30C (59-86F)
- Avoid freezing and excessive heat above 40C (104F)

Inactive ingredients

acrylates/C10-30 alkyl acrylate crosspolymer, aminomethyl propanol, glycerin, water

Package Label - Principal Display Panel

60 mL NDC: 72686-182-03